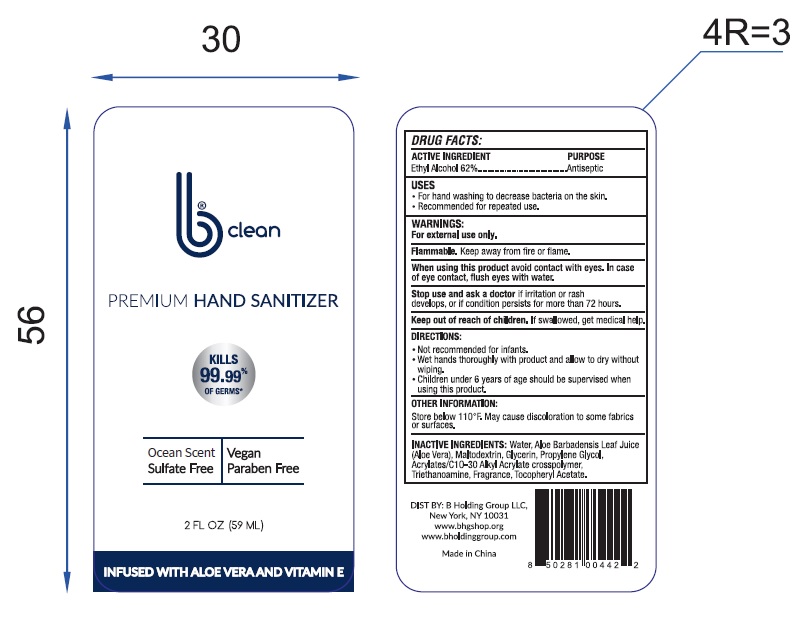 DRUG LABEL: b Clean Premium Hand Sanitizer
NDC: 78396-001 | Form: GEL
Manufacturer: B Holding Group LLC
Category: otc | Type: HUMAN OTC DRUG LABEL
Date: 20200526

ACTIVE INGREDIENTS: ALCOHOL 62 mL/100 mL
INACTIVE INGREDIENTS: TROLAMINE; PROPYLENE GLYCOL; CARBOMER INTERPOLYMER TYPE A (55000 CPS); MALTODEXTRIN; GLYCERIN; ALOE VERA LEAF; WATER; .ALPHA.-TOCOPHEROL ACETATE

This is a hand sanitizer manufactured according to the Temporary Policy for Preparation of Certain Alcohol-Based Hand Sanitizer Products During the Public Health Emergency (CoViD-19); Guidance for Industry.

1. Ethyl Alcohol (62%, v/v)
2. Water (36.228% v/v).
3. ALOE Barbadensis Leaf Juice
4. Maltodextrin
5. Glycerin
6. Propylene Glycol
7. Fragrance
8. Acrylates/c10-30 Alkyl Arcylate Crosspolymer
9. Triethanomine
10. Tocopheryl Acetate

Active Ingredient(s)

Ethyl Alcohol 62% v/v. Purpose: Antiseptic

Purpose

Antiseptic, Hand Sanitizer

Use

Hand Sanitizer to help reduce bacteria that potentially can cause disease. For use when soap and water are not available.

Warnings

For external use only. Flammable. Keep away from heat or flame

Do not use

- in children less than 2 months of age
- on open skin wounds

When using this product keep out of eyes, ears, and mouth. In case of contact with eyes, rinse eyes thoroughly with water.
Stop use and ask a doctor if irritation or rash occurs. These may be signs of a serious condition.
Keep out of reach of children. If swallowed, get medical help or contact a Poison Control Center right away.

Stop use and ask a doctor if irritation or rash occurs. These may be signs of a serious condition.

Keep out of reach of children. If swallowed, get medical help or contact a Poison Control Center right away.

Directions

- Place enough product on hands to cover all surfaces. Rub hands together until dry.
- Supervise children under 6 years of age when using this product to avoid swallowing.

Other information

- Do not store above 110°F
- May discolor some fabrics

Inactive ingredients

Water (36.228% v/v).
ALOE Barbadensis Leaf Juice
Maltodextrin
Glycerin
Propylene Glycol
Fragrance
Acrylates/c10-30 Alkyl Arcylate Crosspolymer
Triethanomine
Tocopheryl Acetate